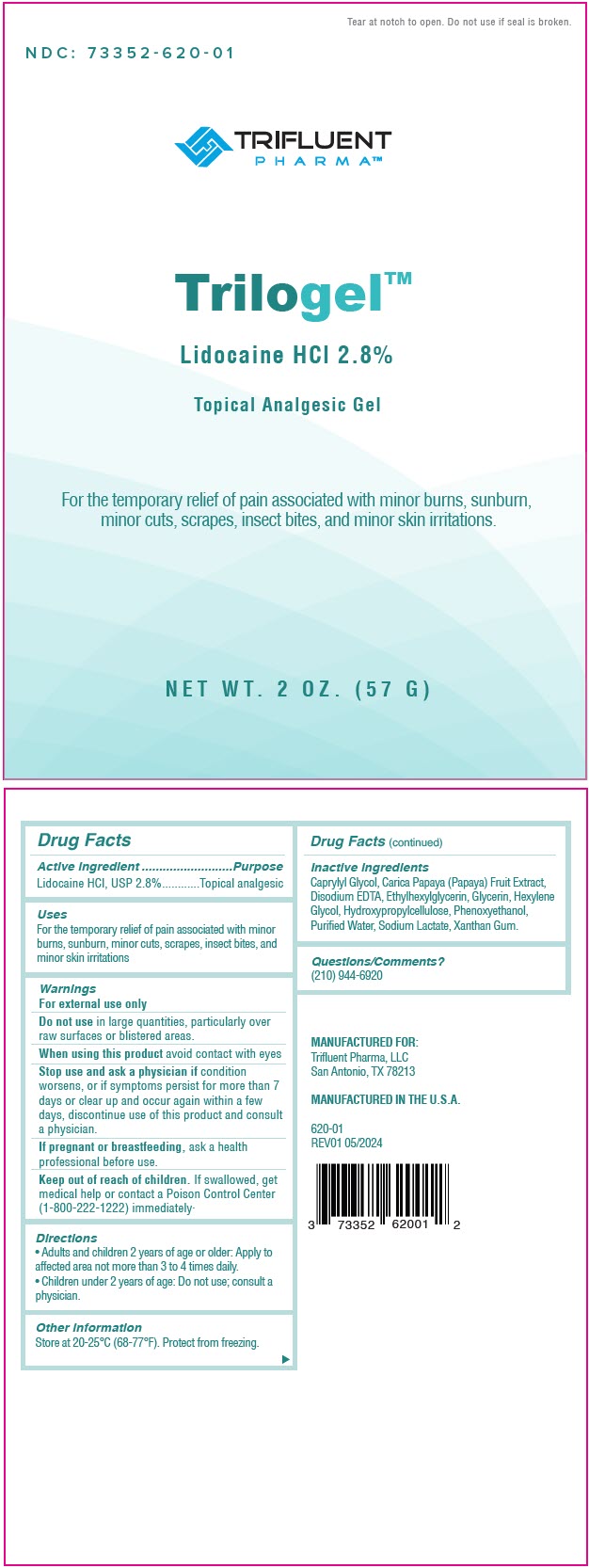 DRUG LABEL: Trilogel
NDC: 73352-620 | Form: GEL
Manufacturer: Trifluent Pharma LLC
Category: otc | Type: HUMAN OTC DRUG LABEL
Date: 20251014

ACTIVE INGREDIENTS: LIDOCAINE HYDROCHLORIDE 28 mg/1 g
INACTIVE INGREDIENTS: WATER; EDETATE DISODIUM; XANTHAN GUM; GLYCERIN; HYDROXYPROPYL CELLULOSE, UNSPECIFIED; PAPAYA; PHENOXYETHANOL; CAPRYLYL GLYCOL; ETHYLHEXYLGLYCERIN; HEXYLENE GLYCOL; SODIUM LACTATE

Trilogel™

Drug Facts

Active Ingredient

Lidocaine HCl, USP 2.8%

Purpose

Topical analgesic

Uses

For the temporary relief of pain associated with minor burns, sunburn, minor cuts, scrapes, insect bites, and minor skin irritations.

Warnings

For external use only

Do not use in large quantities, particularly over raw surfaces or blistered areas.

When using this product avoid contact with eyes

Stop use and ask a physician if condition worsens, or if symptoms persist for more than 7 days or clear up and occur again within a few days, discontinue use of this product and consult a physician.

PREGNANCY OR BREAST FEEDING

If pregnant or breastfeeding, ask a health professional before use.

Keep out of reach of children. If swallowed, get medical help or contact a Poison Control Center (1-800-222-1222) immediately.

Directions

- Adults and children 2 years of age and older: Apply to affected area not more than 3 to 4 times daily.
- Children under 2 years of age: Do not use; consult a physician.

Other Information

Store at 20-25°C (68-77°F). Protect from freezing.

Inactive Ingredients

Caprylyl Glycol, Carica Papaya (Papaya) Fruit Extract, Disodium EDTA, Ethylhexylglycerin, Glycerin, Hexylene Glycol, Hydroxypropylcellulose, Phenoxyethanol, Purified Water, Sodium Lactate, Xanthan Gum.

Questions or Comments?

(210) 944-6920

PRINCIPAL DISPLAY PANEL - 57 G Pouch Label

Tear at notch to open. Do not use if seal is broken.

NDC: 73352-620-01

TRIFLUENT
PHARMA™

Trilogel™

Lidocaine HCl 2.8%

Topical Analgesic Gel

For the temporary relief of pain associated with minor burns, sunburn,
minor cuts, scrapes, insect bites, and minor skin irritations.

NET WT. 2 OZ. (57 G)